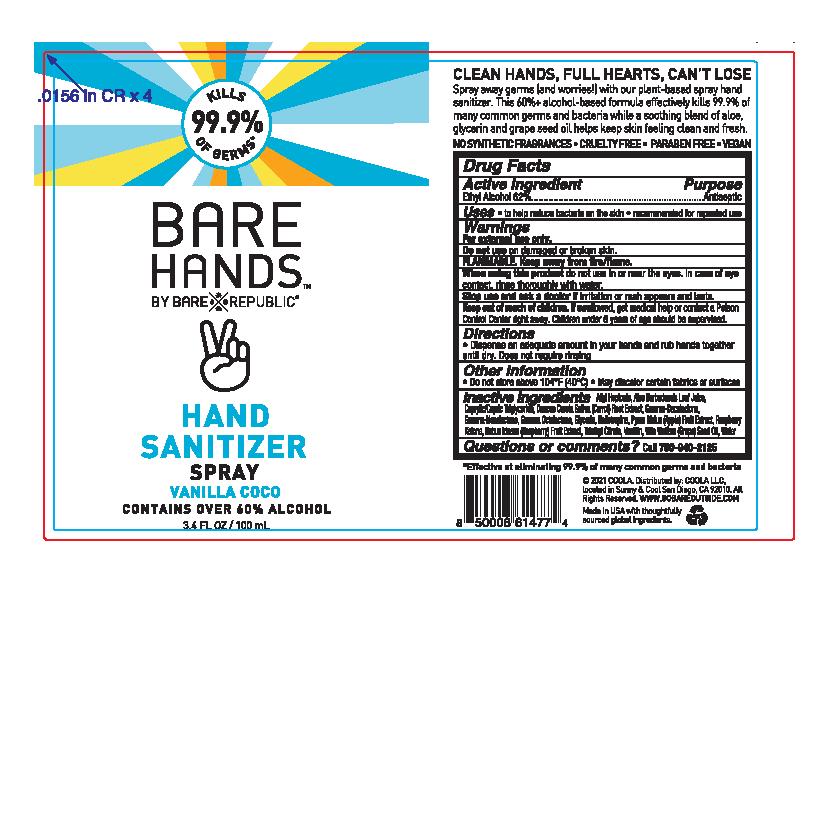 DRUG LABEL: Bare Republic Bare Hands
NDC: 79753-005 | Form: SPRAY
Manufacturer: COOLA LLC
Category: otc | Type: HUMAN OTC DRUG LABEL
Date: 20201120

ACTIVE INGREDIENTS: ALCOHOL 62 mL/100 mL
INACTIVE INGREDIENTS: .GAMMA.-NONALACTONE; ALLYL HEPTANOATE; .GAMMA.-DECALACTONE; .GAMMA.-OCTALACTONE; GLYCERIN; PIPERONAL; GRAPE SEED OIL; WATER; TRIETHYL CITRATE; 4-(P-HYDROXYPHENYL)-2-BUTANONE; VANILLIN; CARROT; APPLE; MEDIUM-CHAIN TRIGLYCERIDES; ALOE VERA LEAF; RASPBERRY

Bare Republic Bare Hands Hand Sanitizer Spray 3.4oz - Vanilla Coco

Active Ingredient

Ehtyl Alcohol 62%

Purpose

Antiseptic

Uses

to help reduce bacteria on the skin

recommended for repeated use

Warnings

For external use only.

Do not use on damaged or broken skin

Flammable. Keep away from fire/flame

When using this product do not use in or near the eyes. In case of eye contact, rinse thoroughly with water.

Stop use and ask a doctor if irritation or rash appears and lasts.

Keep out of reach of children. If swallowed, get medical help or contact a Poison Control Center right away.

Children under 6 years of age should be supervised.

Directions

Dispense an adequate amount in your hands and rub hands together until dry. Does not require rinsing

Other information

Do not store above 104 F (40 C).

May discolor certain fabrics or surfaces

Inactive ingredients

Allyl Heptonate, Aloe Barbadensis Leaf Juice, Caprylic/Capric Triglyceride, Daucus Carota Sativa (Carrot) Root Extract, Gamma-Decalactone, Gamma-Nonalactone, Gamma Octalactone, Glycerin, Heliotropine, Pyrus Malus (Apple) Fruit Extract, Raspberry Ketone, Rubus Idaeus (Raspberry) Fruit Extract, Triethyl Citrate, Vanillin, Vitis Vinifera (Grape) Seed Oil, Water

Questions or comments?

Call 760-940-2125